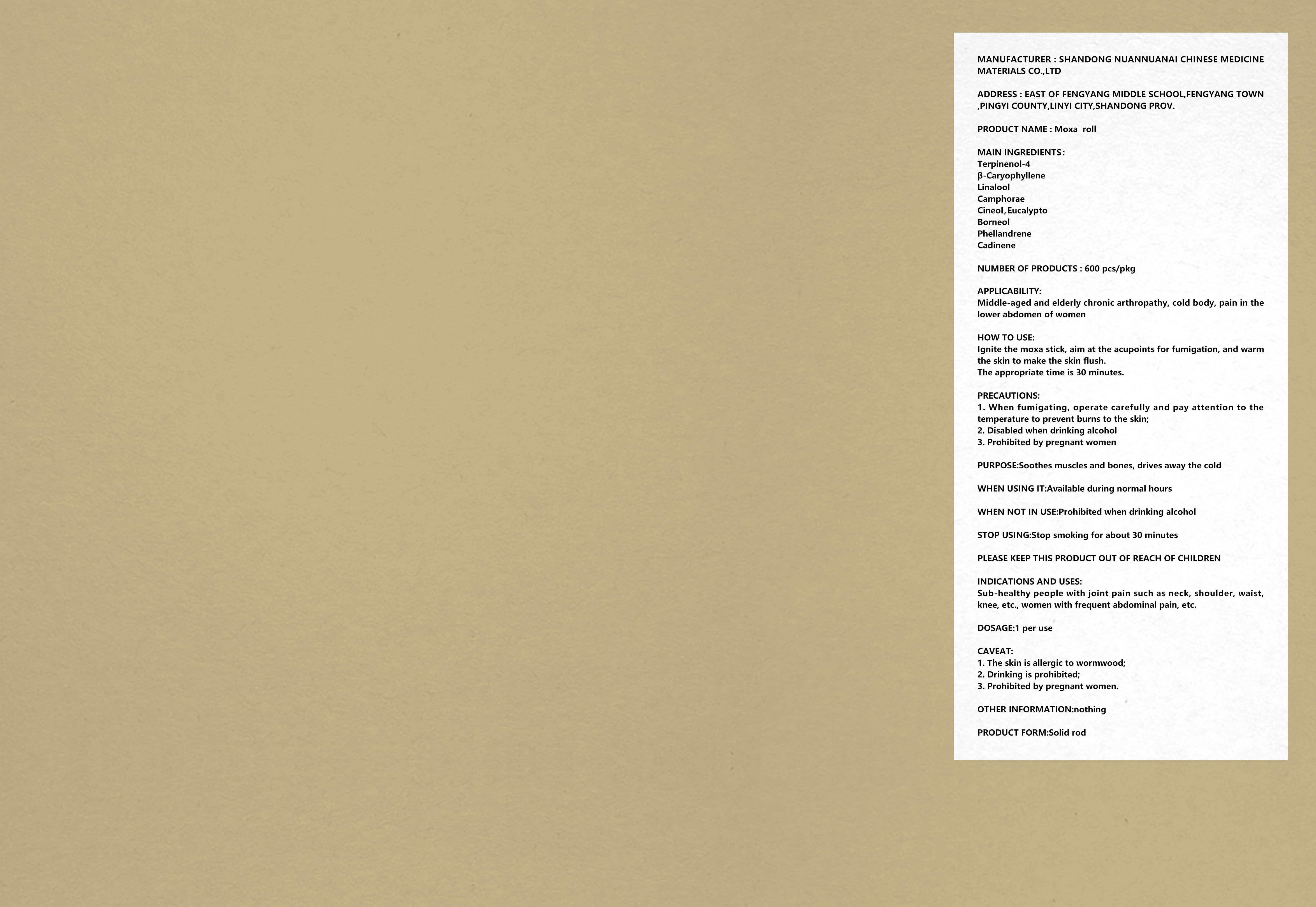 DRUG LABEL: Moxa  roll
NDC: 81654-001 | Form: LIQUID
Manufacturer: Shandong Nuannuanai Chinese Medicinal Materials Import & Export Co., Ltd.
Category: homeopathic | Type: HUMAN OTC DRUG LABEL
Date: 20210303

ACTIVE INGREDIENTS: CARYOPHYLLENE 26 g/100 mL; 4-TERPINEOL, (+/-)- 32 g/100 mL
INACTIVE INGREDIENTS: .ALPHA.-PHELLANDRENE; .ALPHA.-CUBEBENE, (-)-; CAMPHOR (SYNTHETIC); BORNEOL, (+)-; LINALOOL, (+/-)-; EUCALYPTUS OIL

NDICATIONS AND USES

Sub-healthy people with joint pain such as neck, shoulder, waist,knee, etc., women with frequent abdominal pain, etc.

How To USE

lgnite the moxa stick, aim at the acupoints for fumigation, and warmthe skin to make the skin flush.
The appropriate time is 30 minutes.

ACTIVE INGREDIENT

Terpinenol-4

β-Caryophyllene

PURPOSE

Soothes muscles and bones, drives away the cold

WHEN USING

Available during normal hours

Stop smoking for about 30 minutes

KEEP OUT OF REACH OF CHILDREN

PLEASE KEEP THIS PRODUCT oUT OF REACH OF CHILDREN

INACTIVE INGREDIENT

Linalool

Camphorae
Cineol，Eucalypto

Borneol

Phellandrene

Cadinene

WARNINGS

1.The skin is allergic to wormwood;
2.Drinking is prohibited;
3.Prohibited by pregnant women.

STORAGE AND HANDLING

Store in a cool and dry place